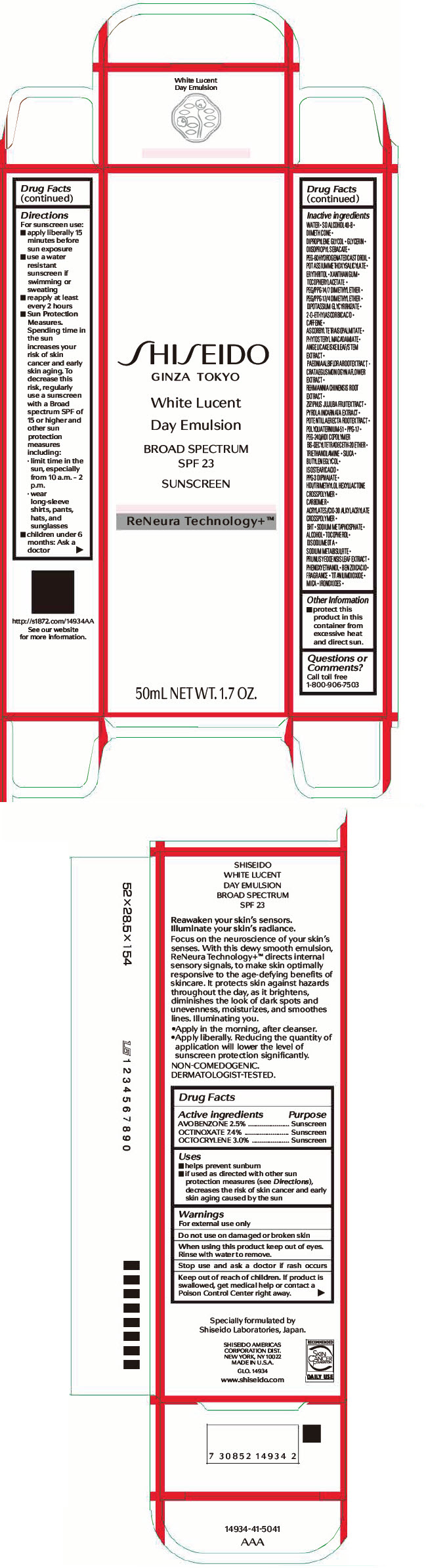 DRUG LABEL: SHISEIDO WHITE LUCENT DAY
NDC: 58411-463 | Form: EMULSION
Manufacturer: SHISEIDO AMERICAS CORPORATION
Category: otc | Type: HUMAN OTC DRUG LABEL
Date: 20260106

ACTIVE INGREDIENTS: AVOBENZONE 1.285 g/50 mL; OCTINOXATE 3.8036 g/50 mL; OCTOCRYLENE 1.542 g/50 mL
INACTIVE INGREDIENTS: PRUNUS X YEDOENSIS LEAF; PHENOXYETHANOL; BENZOIC ACID; TITANIUM DIOXIDE; MICA; FERRIC OXIDE RED; FERRIC OXIDE YELLOW; FERROSOFERRIC OXIDE; WATER; DIMETHICONE; DIPROPYLENE GLYCOL; GLYCERIN; DIISOPROPYL SEBACATE; PEG-60 HYDROGENATED CASTOR OIL; POTASSIUM METHOXYSALICYLATE; ERYTHRITOL; XANTHAN GUM; .ALPHA.-TOCOPHEROL ACETATE, DL-; PEG/PPG-14/7 DIMETHYL ETHER; PEG/PPG-17/4 DIMETHYL ETHER; GLYCYRRHIZINATE DIPOTASSIUM; 2-O-ETHYL ASCORBIC ACID; CAFFEINE; ASCORBYL TETRAISOPALMITATE; PHYTOSTERYL MACADAMIATE; ANGELICA KEISKEI TOP; PAEONIA LACTIFLORA ROOT; CRATAEGUS MONOGYNA FLOWER; REHMANNIA GLUTINOSA ROOT; JUJUBE FRUIT; POTENTILLA ERECTA ROOT; POLYQUATERNIUM-51 (2-METHACRYLOYLOXYETHYL PHOSPHORYLCHOLINE/N-BUTYL METHACRYLATE; 3:7); PPG-17; TROLAMINE; SILICON DIOXIDE; BUTYLENE GLYCOL; ISOSTEARIC ACID; HEXAMETHYLENE DIISOCYANATE/TRIMETHYLOL HEXYLLACTONE CROSSPOLYMER; CARBOMER HOMOPOLYMER, UNSPECIFIED TYPE; CARBOMER INTERPOLYMER TYPE A (ALLYL SUCROSE CROSSLINKED); BUTYLATED HYDROXYTOLUENE; SODIUM POLYMETAPHOSPHATE; ALCOHOL; .ALPHA.-TOCOPHEROL; EDETATE DISODIUM; SODIUM METABISULFITE

SHISEIDO WHITE LUCENT DAY EMULSION

Drug Facts

ACTIVE INGREDIENT

Active ingredients | Purpose
Avobenzone 2.5% | Sunscreen
Octinoxate 7.4% | Sunscreen
Octocrylene 3.0% | Sunscreen

Uses

- helps prevent sunburn
- if used as directed with other sun protection measures (see Directions), decreases the risk of skin cancer and early skin aging caused by the sun

Warnings

For external use only

Do not use on damaged or broken skin

WHEN USING

When using this productkeep out of eyes. Rinse with water to remove.

Stop use and ask a doctorif rash occurs.

Keep out of reach of children.If product is swallowed, get medical help or contact a Poison Control Center right away.

Directions

For sunscreen use:

- apply liberally 15 minutes before sun exposure
- use a water resistant sunscreen if swimming or sweating
- reapply at least every 2 hours
- children under 6 months: ask a doctor
- Sun Protection Measures. Spending time in the sun increases your risk of skin cancer and early skin aging. To decrease this risk, regularly use a sunscreen with a broad spectrum SPF of 15 or higher and other sun protection measures including:
  - limit time in the sun, especially from 10 a.m. – 2 p.m.
  - wear long-sleeve shirts, pants, hats, and sunglasses

Inactive Ingredients

Water, SD Alcohol 40-B, Dimethicone, Dipropylene Glycol, Glycerin, Diisopropyl Sbeacate, Peg-60 Hydrogenated Castor Oil, Potassium Methoxysalicylate, Erythritol, Xanthan Gum, Tocopheryl Acetate, Peg/PPG-14/7 Dimethyl Ether, Peg/PPG-17/4 Dimethyl Ether, Dipotassium Glycyrrhizate, 2-O-Ethyl Ascorbic Acid, Caffeine, Ascorbyl Tetraisopalmitate, Phytosteryl Macadamiate, Angelica Keiskei Leaf/Stem Extract, Paeonia Albiflora Root Extract, Cratagus Monogyna Flower Extract, Rehmannia Chinesis Root Extract, Ziziphu Jujuba Fruit Extract, Polyquaternium 51, PPG-17, Peg-240/HDI Copolymer BIS-Decyltetradeceth-20 Ether, Triethanolamine, Silica, Butylene Glycol, Isostearic Acid, PPG-3 Dipivalate, HDI/Trimethylol Hexyllactone Crosspolymer, Carbomer, Acrylates/C10-30 Alkyl Acrylate Crosspolymer, BHT, Sodium Metaphosphate, Alcohol, Tocopherol, Disodium EDTA, Sodium Metabisulfite, Prunus Yedoensis Leaf Extract, Phenoxyethanol, Benzoic Acid, Fragrance, Titanium Dioxide, Mica, Iron Oxides

Other information

Protect this product in this container from excessive heat and direct sun.

Questions or comments?

Call toll free 1-800-906-7503

PRINCIPAL DISPLAY PANEL - 50 mL Tube Carton

SHISEIDO
GINZA TOKYO

White Lucent

Day Emulsion

BROAD SPECTRUM
SPF 23

SUNSCREEN

ReNeura Technology+™

50mL NET WT. 1.7 OZ.